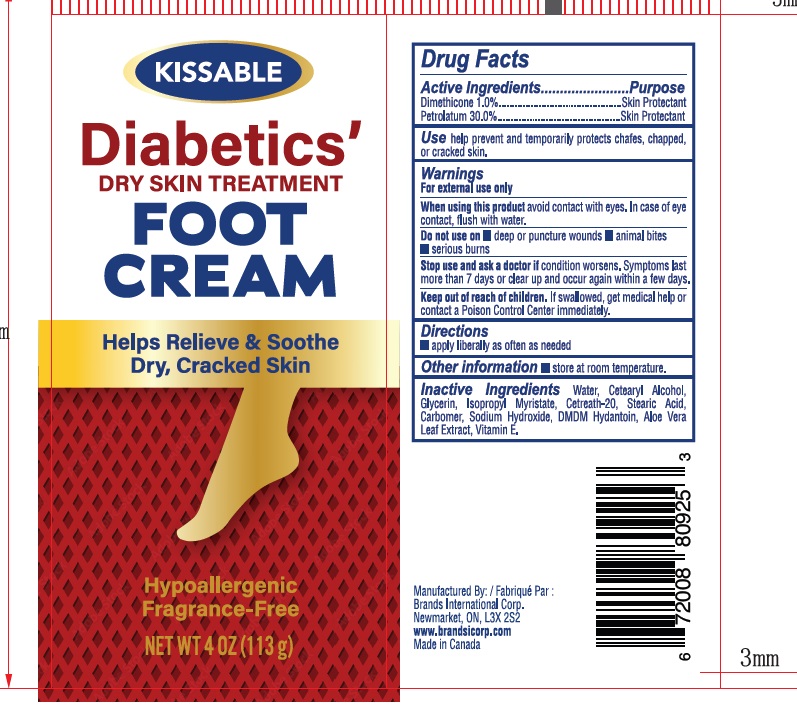 DRUG LABEL: Diabetics Foot Cream
NDC: 50157-610 | Form: LOTION
Manufacturer: BRANDS INTERNATIONAL
Category: otc | Type: HUMAN OTC DRUG LABEL
Date: 20230222

ACTIVE INGREDIENTS: PETROLATUM 30 g/100 g; DIMETHICONE 1 g/100 g
INACTIVE INGREDIENTS: ALOE VERA LEAF; WATER; GLYCERIN; DMDM HYDANTOIN; LAURETH-7; SODIUM HYDROXIDE; CETOSTEARYL ALCOHOL; CARBOMER 1342; .ALPHA.-ELEOSTEARIC ACID; ISOPROPYL MYRISTATE; VITAMIN E POLYETHYLENE GLYCOL SUCCINATE

KISSABLE -Diabetics' Foot Cream 4 oz

Active Ingredient Purpose

Dimethicone 1% ...... Skin Protectant

Petrolatum 30%........Skin Protectant

PURPOSE

Skin protectant

Keep out of reach of children. If swallowed, get medical help or contact a Poison Control Center immediately.

INDICATIONS AND USAGE

Use help prevent and temporarily protets chafed, chapped, or cracked skin.

Warnings For external use only.

When using this product avoid contact with eyes. In case of eye contact, flush with water.

Do not use on

- deep or puncture wounds
- animal bites
- serious burns

Stop use and ask a doctor if condition worsens. Symptoms last more than 7 days or clear up and occur again within a few days.

DOSAGE AND ADMINISTRATION

Directions apply liberally as often as needed.

Other information Store at room temperature.

INACTIVE INGREDIENT

Inactive Ingredients Water, Ceterayl Alcohol, Glycerin, Isopropyl Myristate, DMDM Hydantoin, Carbomer, Sodium Hydroxide, Aloe Vera Leaf , Vitamin E.